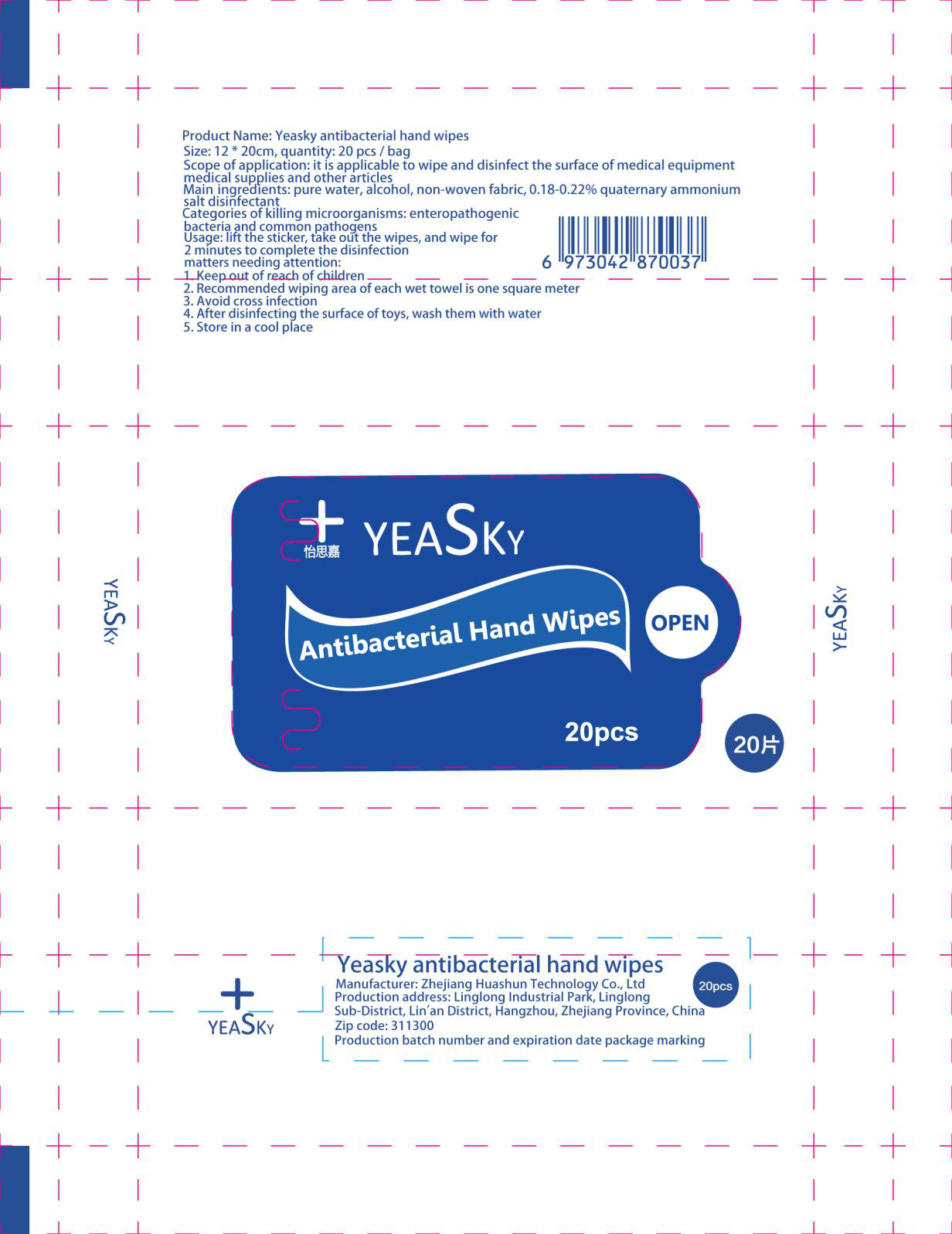 DRUG LABEL: Yeasky antibacterial hand wipes
NDC: 77046-008 | Form: CLOTH
Manufacturer: Zhejiang huashun technology co. LTD
Category: otc | Type: HUMAN OTC DRUG LABEL
Date: 20200726

ACTIVE INGREDIENTS: DIDECYLDIMONIUM CHLORIDE 0.12 g/20 1; BENZALKONIUM CHLORIDE 0.12 g/20 1
INACTIVE INGREDIENTS: BRONOPOL; GLYCERIN; WATER; ETHYLHEXYLGLYCERIN; PROPYLENE GLYCOL

DOSAGE AND ADMINISTRATION

Store in a cool, dry place, between 15°to 25°, avoid freezing and excessive heat above 40°.

INACTIVE INGREDIENT

Purified Water，Bronopol，Ethylhexylglycerin，Propylene Glycol，Glycerin

INDICATIONS AND USAGE

lift the sticker, take out the wipes, and wipe for 2 minutes to complete the disinfection.

ACTIVE INGREDIENT

Benzalkonium Chloride,Didecyldimonium Chloride

keep out of reach of children

PURPOSE

Disinfection
Sterilization
No Rinseing

WARNINGS

1 Keep out of reach of children.
2. Recommended wiping area of each wet towel is one square meter
3. Avoid cross infection
4. After disinfecting the surface of toys, wash them with water
5. Store in a cool place